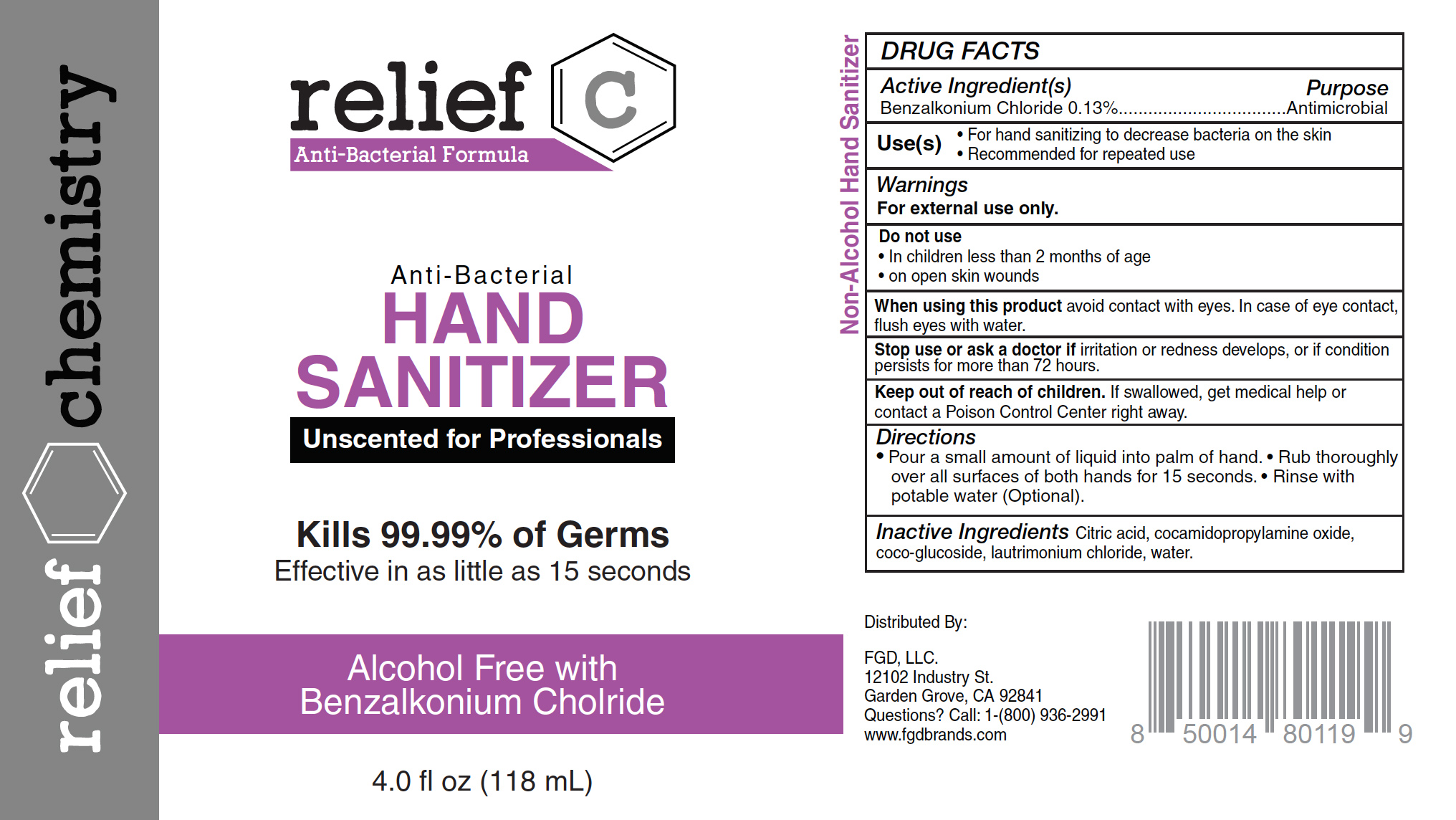 DRUG LABEL: Relief C Anti-Bacterial Formula Anti-Bacterial Hand Sanitizer
NDC: 73787-108 | Form: LIQUID
Manufacturer: FGD, LLC
Category: otc | Type: HUMAN OTC DRUG LABEL
Date: 20210106

ACTIVE INGREDIENTS: BENZALKONIUM CHLORIDE 0.13 g/100 mL
INACTIVE INGREDIENTS: CITRIC ACID MONOHYDRATE; WATER; COCO GLUCOSIDE; LAURTRIMONIUM CHLORIDE; COCAMIDOPROPYLAMINE OXIDE

Relief C Anti-Bacterial Formula Anti-Bacterial Hand Sanitizer

Active ingredient

Benzalkonium Chloride 0.13%

Purpose

Antimicrobial

Directions

▪ Pump a small amount of foam into palm of hand

▪ Rub thoroughly over all surfaces of both hands for 15 seconds

▪ Rinse with potable water

Keep out of reach of children

If swallowed, get medical help or contact a Poison Control Center right away.

Warnings

For external use only

When using this product avoid contact with eyes. In case of eye contact, flush eyes with water.

Stop use and ask a doctor if irritation or redness develops, or if condition persists for more than 72 hours.

Uses

For hand washing to decrease bacteria on the skin

Recommended for repeated use

Inactive ingredients

Water, coco-glucoside, laurtrimonium chloride, cocamidopropylamine oxide, citric acid